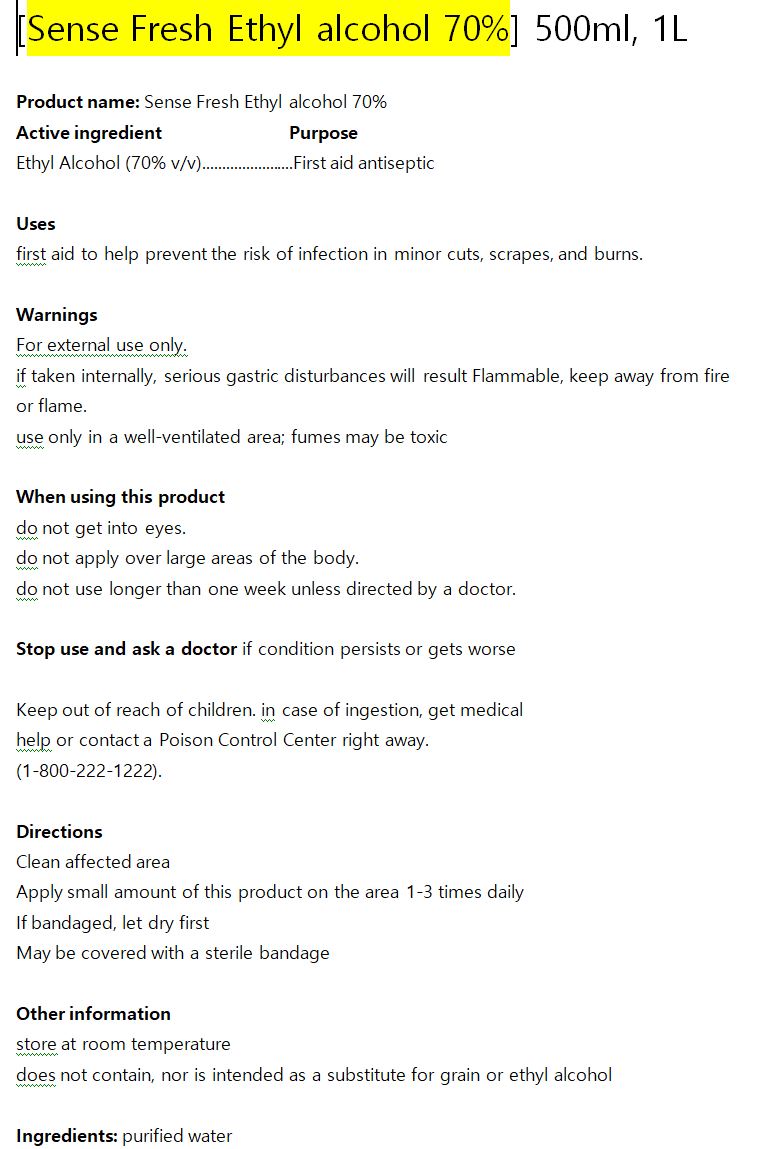 DRUG LABEL: Sense Fresh Ethyl alcohol 70%
NDC: 74085-0004 | Form: LIQUID
Manufacturer: BIOCHEM KOREA CO LTD
Category: otc | Type: HUMAN OTC DRUG LABEL
Date: 20201224

ACTIVE INGREDIENTS: ALCOHOL 70 g/100 mL
INACTIVE INGREDIENTS: WATER

Drug Facts

ACTIVE INGREDIENT

ethyl alcohol

PURPOSE

first aid to help prevent the risk of infection in minor cuts, scrapes, and burns.

KEEP OUT OF REACH OF THE CHILDREN

INDICATIONS AND USAGE

Clean affected area

Apply small amount of this product on the area 1-3 times daily

If bandaged, let dry first

May be covered with a sterile bandage

WARNINGS

■ For external use only.

■ Do not use in eyes.

■ lf swallowed, get medical help promptly.

■ Stop use, ask doctor lf irritation occurs.

■ Keep out of reach of children.

DOSAGE AND ADMINISTRATION

for external use only

INACTIVE INGREDIENT

Water, Isopropyl Alcohol, Aloe Barbadensis Leaf Juice, propolis extract, Caprylyl Glycol, Glycerin, Isopropyl Myristate, Tocopheryl Acetate, Acrylates C10 30 Alkyl Acrylate Crosspolymer, Aminomethyl Propanol, Fragrance